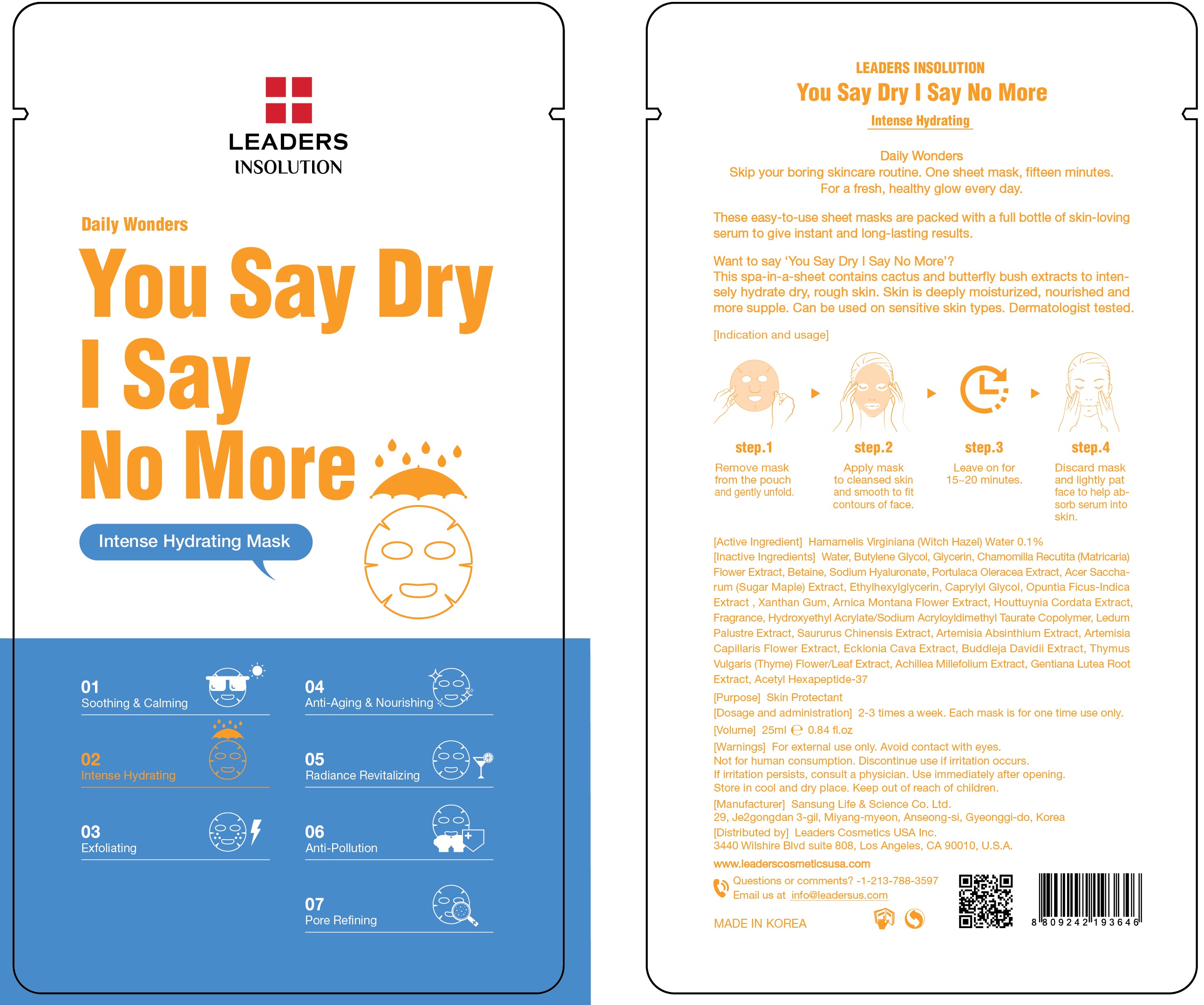 DRUG LABEL: Leaders Daily Wonders You Say Dry I Say No More
NDC: 69424-420 | Form: PATCH
Manufacturer: SANSUNG LIFE & SCIENCE CO., LTD.
Category: otc | Type: HUMAN OTC DRUG LABEL
Date: 20160129

ACTIVE INGREDIENTS: Witch Hazel 25 mg/25 mL
INACTIVE INGREDIENTS: Water; Butylene Glycol

ACTIVE INGREDIENT

[Active Ingredient] Hamamelis Virginiana (Witch Hazel) Water 0.1%

INACTIVE INGREDIENT

[Inactive Ingredients] Water, Butylene Glycol, Glycerin, Chamomilla Recutita (Matricaria) Flower Extract, Betaine, Sodium Hyaluronate, Portulaca Oleracea Extract, Acer Saccharum (Sugar Maple) Extract, Ethylhexylglycerin Caprylyl Glycol, Opuntia Ficus-Indica Extract , Xanthan Gum, Arnica Montana Flower Extract, Houttuynia Cordata Extract, Fragrance, Hydroxyethyl Acrylate/Sodium Acryloyldimethyl Taurate Copolymer, Ledum Palustre Extract, Saururus Chinensis Extract, Artemisia Absinthium Extract, Artemisia Capillaris Flower Extract, Ecklonia Cava Extract, Buddleja Davidii Extract, Thymus Vulgaris (Thyme) Flower/Leaf Extract, Achillea Millefolium Extract, Gentiana Lutea Root Extract, Acetyl Hexapeptide-37

PURPOSE

[Purpose] Skin Protectant

WARNINGS

[Warnings] For external use only. Avoid contact with eyes. Not for human consumption. Discontinue use if irritation occurs. If irritation persists, consult a physician. Use immediately after opening. Store in cool and dry place. Keep out of reach of children.

KEEP OUT OF REACH OF CHILDREN

INDICATIONS & USAGE

[Indication and usage]

Step 1. Remove mask from the pouch and gently unfold.

Step 2. Apply mask to cleansed skin and smooth to fit contours of face.

Step 3. Leave on for 15~20 minutes.

Step 4. Discard mask and lightly pat face to help absorb serum into skin.

DOSAGE & ADMINISTRATION

[Dosage and administration] 2-3 times a week. Each mask is for one time use only.